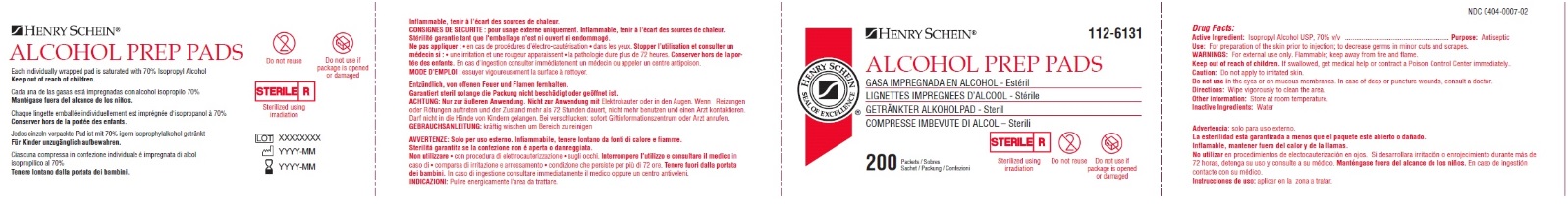 DRUG LABEL: Alcohol Prep Pads
NDC: 0404-0007 | Form: SWAB
Manufacturer: Henry Schein, Inc.
Category: otc | Type: HUMAN OTC DRUG LABEL
Date: 20251023

ACTIVE INGREDIENTS: ISOPROPYL ALCOHOL 70 mL/100 mL
INACTIVE INGREDIENTS: WATER

Henry Schein Medium APP

Active Ingredient

Isopropyl Alcohol USP, 70% v/v

Purpose

Antiseptic

Use:

For preparation of the skin prior to injection; to decrease germs in minor cuts and scrapes.

WARNINGS:

- For external use only. Flammable; keep away from fire and flame.

Keep out of reach of children.

If swallowed, get medical help or contact a Poison Control Center immediately.

Caution:

Do not apply to irritated skin.

Do not use

in the eyes, or on mucous membranes. In case of deep or puncture wounds, consult a doctor.

Directions:

Wipe vigorously to clean the area.

Other information:

Store at room temperature.

Inactive ingredient:

Water

Principal Display Panel

HENRY SCHEIN 112-6131

ALCOHOL PREP PADS

NDC 0404-0007-02

200 Packets/Sobres

Sachets/Packung/Confezioni

STERILE

Sterilized using irridiation

Do not reuse

Do not use if package is opened or damaged